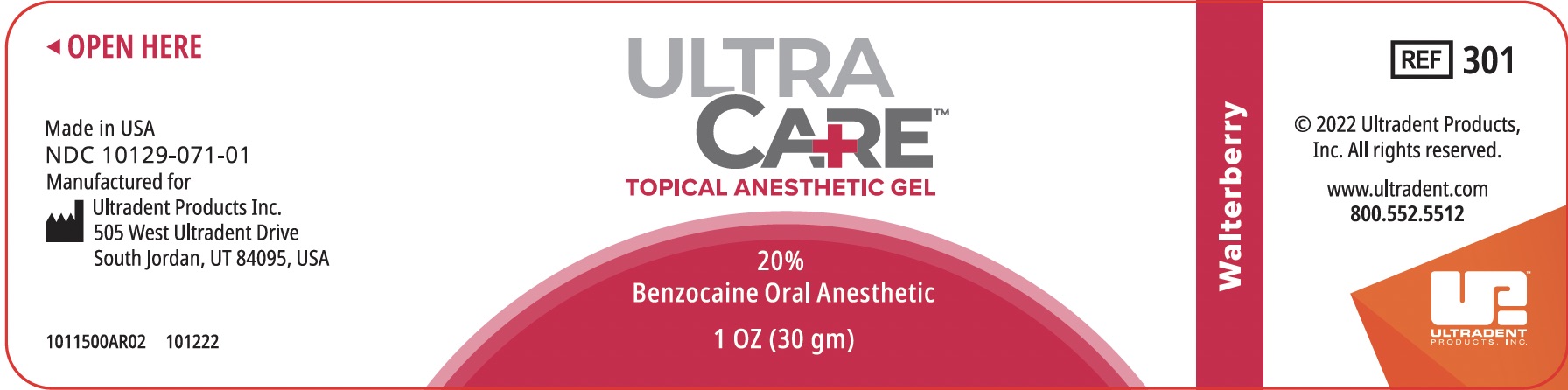 DRUG LABEL: UltraCare Anesthetic Gel
NDC: 10129-071 | Form: GEL
Manufacturer: The Bellport Company, Inc. dba Gingi-Pak
Category: otc | Type: HUMAN OTC DRUG LABEL
Date: 20250129

ACTIVE INGREDIENTS: BENZOCAINE 200 mg/1 g
INACTIVE INGREDIENTS: POLYETHYLENE GLYCOL 400; POTASSIUM SODIUM SACCHARATE; POLYETHYLENE GLYCOL 3350

UltraCare

Active Ingredient

Benzocaine 20% w/v

Warnings

For external use only.

Stop use and ask a doctor if

- Sore throat is severe and more than 2 days

- Fever, headache, rash, nausea, or vomiting develops

- Mouth sore does not go away within 10 days

- Irritation, pain or redness worsens

Ask a doctor (pharmacist) before use if you have severely traumatized, infected mucosal areas or areas of the posterior pharynx that might obtund protective reflexes.

Methemoglobinemia warning

Use of this product may cause methemoglobinemia, a rare but serious condition that must be treated prompltly because it reduces the amount of oxygen carried in blood. Cease use and seek immediate medical attention if one of the following symptoms develops: -Pale, gray, or blue colored skin (cyanosis) - Headache - Rapid heart rate - Shortness of breath _ Dizziness or lightheadedness - Fatigue or lack of energy

Do not use in patients with history of hypersensitivity to any ester-type local anesthetics. Do not use the product for teething or in infants and children younger than 2 years.

Do not use if you have history of allergy to any "caine" local anesthetics.

Avoid contact with eyes.

Keep out of reach of children.

OVERDOSAGE

If more than normal usage amount if accidentally swallowed, get medical help or contact a Poison Control Center immediately. Do not exceed recommended dosage.

Purpose

Oral Anesthetic

Uses

Reduce pain or discomfort caused by - minor dental procedures - minor gum injury - canker sores - sore throat - minor mouth or gum irritations caused by dentures or orthodontic applicances

Indications

Anesthesia of mucous membrane of oropharynx. Minimizes the pain of ulcers, needle puncture, deep scaling procedures, and the application of matrix bands. Also an aid in the taking of impressions or intraoral radiographs of patients with an excessive gag reflexes.

Dosage and Administration

Mucosa should be dried prior to application. Removal of excess saliva with cotton rolls or saliva ejectors will minimize dilution of the local anesthetic. Sterile cotton or gauze should be used in applying anesthetic to mucosa. Care must be taken to avoid cross-contamination between patients. Total dose should not exceed the amout required for anethesia.

- Apply to the affected area.

- Remain in place for at least 1 minute and then spit.

- Use up to 4 times daily or as directed by a dentist or doctor.

- Do not exceed recommended dosage.

- This product is for adultsand children 2 years of age and older.

- Chidlren under 2 years of age should consult a dentist or a doctor.

Other information

Inactive Ingredients

Polyethylene Glycol 400 (PEG 400) NF, Polyethylene Glycol 3350 (3550) NF, Sodium Saccharin, natural and artificial flavors.

Storage

Avoid excessive heat above 40C (104F).

Net content 1oz. (30 grams)